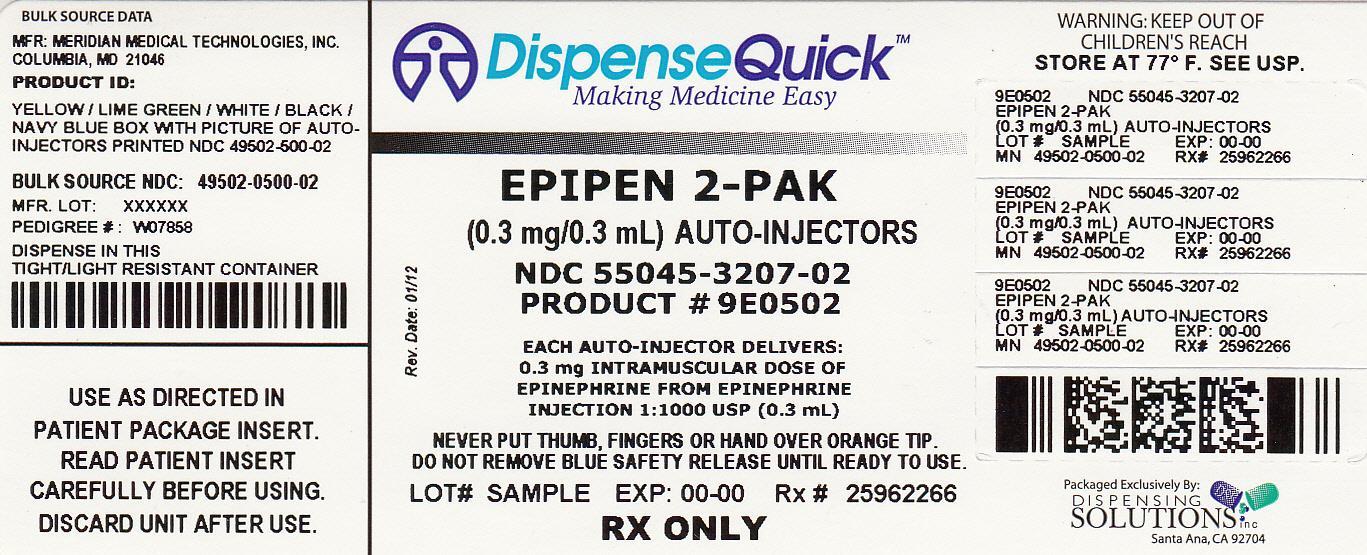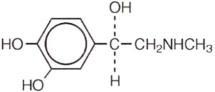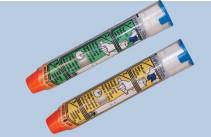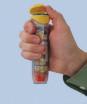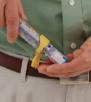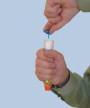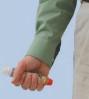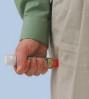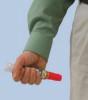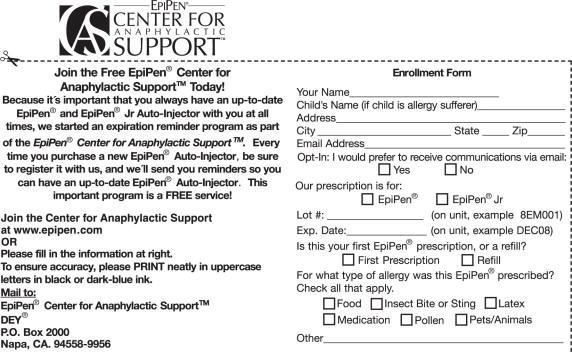 DRUG LABEL: EpiPen
NDC: 55045-3207 | Form: INJECTION
Manufacturer: Dispensing Solutions, Inc.
Category: prescription | Type: HUMAN PRESCRIPTION DRUG LABEL
Date: 20120925

ACTIVE INGREDIENTS: Epinephrine 0.3 mg/0.3 mL
INACTIVE INGREDIENTS: Sodium Chloride; Sodium Metabisulfite; Water; Hydrochloric Acid; Nitrogen

EpiPen®
(epinephrine) Auto-Injector 0.3 mg
EpiPen® = one dose of 0.30 mg epinephrine (USP, 1:1000, 0.3 mL)
EpiPen® JR
(epinephrine) Auto-Injector 0.15 mg
EpiPen® Jr = one dose of 0.15 mg epinephrine (USP, 1:2000, 0.3 mL)

DESCRIPTION

Each EpiPen® Auto-Injector delivers a single dose of 0.3 mg epinephrine injection, USP, 1:1000 (0.3 mL) in a sterile solution.

Each EpiPen® Jr Auto-Injector delivers a single dose of 0.15 mg epinephrine injection, USP, 1:2000 (0.3 mL) in a sterile solution.

The EpiPen® and EpiPen® Jr Auto-Injectors each contain 2 mL epinephrine solution. Approximately 1.7 mL remains in the auto-injector after activation and cannot be used.

Each 0.3 mL in the EpiPen® Auto-Injector contains 0.3 mg epinephrine, 1.8 mg sodium chloride, 0.5 mg sodium metabisulfite, hydrochloric acid to adjust pH, and Water for Injection.
The pH range is 2.2-5.0. Each 0.3 mL in the EpiPen® Jr Auto-Injector contains 0.15 mg epinephrine, 1.8 mg sodium chloride, 0.5 mg sodium metabisulfite, hydrochloric acid to adjust pH, and Water for Injection. The pH range is 2.2-5.0.

Epinephrine is a sympathomimetic catecholamine. Chemically, epinephrine is B-(3, 4-dihydroxyphenyl)-a-methyl-aminoethanol, with the following structure:

Epinephrine solution deteriorates rapidly on exposure to air or light, turning pink from oxidation to adrenochrome and brown from the formation of melanin. Replace EpiPen® and EpiPen® Jr Auto-Injectors if the epinephrine solution appears discolored.

EpiPen® and EpiPen® Jr Auto-Injectors do not contain latex.

CLINICAL PHARMACOLOGY

Epinephrine is the drug of choice for the emergency treatment of severe allergic reactions (Type I) to insect stings or bites, foods, drugs, and other allergens. It can also be used in the treatment of anaphylaxis of unknown cause (idiopathic anaphylaxis) or exercise-induced anaphylaxis. When given intramuscularly or subcutaneously it has a rapid onset and short duration of action. Epinephrine acts on both alpha and beta adrenergic receptors. Through its action on alpha adrenergic receptors, epinephrine lessens the vasodilation and increased vascular permeability that occurs during anaphylaxis, which can lead to loss of intravascular fluid volume and hypotension. Through its action on beta-adrenergic receptors, epinephrine causes bronchial smooth muscle relaxation that helps alleviate bronchospasm, wheezing and dyspnea that may occur during anaphylaxis. Epinephrine also alleviates pruritus, urticaria, and angioedema and may be effective in relieving gastrointestinal and genitourinary symptoms associated with anaphylaxis because of its relaxer effects on the smooth muscle of the stomach, intestine, uterus, and urinary bladder.

INDICATIONS AND USAGE

EpiPen® and EpiPen® Jr Auto-Injectors are indicated in the emergency treatment of allergic reactions (Type I) including anaphylaxis to stinging insects (e.g., order Hymenoptera, which include bees, wasps, hornets, yellow jackets and fire ants) and biting insects (e.g., triatoma, mosquitos), allergen immunotherapy, foods, drugs, diagnostic testing substances (e.g., radiocontrast media) and other allergens, as well as idiopathic anaphylaxis or exercise-induced anaphylaxis. EpiPen® and EpiPen® Jr Auto-Injectors are intended for immediate administration in patients, who are determined to be at increased risk for anaphylaxis, including individuals with a history of anaphylactic reactions. Selection of the appropriate dosage strength is determined according to patient body weight (see DOSAGE AND ADMINISTRATION section).

Such reactions may occur within minutes after exposure and consist of flushing, apprehension, syncope, tachycardia, thready or unobtainable pulse associated with a fall in blood pressure, convulsions, vomiting, diarrhea and abdominal cramps, involuntary voiding, wheezing, dyspnea due to laryngeal spasm, pruritus, rashes, urticaria or angioedema.

EpiPen® and EpiPen® Jr Auto-Injectors are intended for immediate self-administration as emergency supportive therapy only and are not a substitute for immediate medical care.

CONTRAINDICATIONS

There are no absolute contraindications to the use of epinephrine in a life-threatening situation.

WARNINGS

EpiPen® and EpiPen® Jr Auto-Injectors should only be injected into the anterolateral aspect of the thigh. DO NOT INJECT INTO BUTTOCK. Injection into the buttock may not provide effective treatment of anaphylaxis. Advise the patient to go immediately to the nearest emergency room for further treatment of anaphylaxis.

Since epinephrine is a strong vasoconstrictor, accidental injection into the digits, hands or feet may result in loss of blood flow to the affected area. Treatment should be directed at vasodilation in addition to further treatment of anaphylaxis (see ADVERSE REACTIONS). Advise the patient to go immediately to the nearest emergency room and to inform the healthcare provider in the emergency room of the location of the accidental injection.

DO NOT INJECT INTRAVENOUSLY. Large doses or accidental intravenous injection of epinephrine may result in cerebral hemorrhage due to sharp rise in blood pressure. Rapidly acting vasodilators can counteract the marked pressor effects of epinephrine if there is such inadvertent administration.

Epinephrine is the preferred treatment for serious allergic reactions or other emergency situations even though this product contains sodium metabisulfite, a sulfite that may, in other products, cause allergic-type reactions including anaphylactic symptoms or life-threatening or less severe asthmatic episodes in certain susceptible persons. The alternatives to using epinephrine in a life-threatening situation may not be satisfactory. The presence of a sulfite in this product should not deter administration of the drug for treatment of serious allergic or other emergency situations even if the patient is sulfite-sensitive.

Epinephrine should be administered with caution in patients who have heart disease, including patients with cardiac arrhythmias, coronary artery or organic heart disease, or hypertension. In such patients, or in patients who are on drugs that may sensitize the heart to arrhythmias, e.g., digitalis, diuretics, or anti-arrhythmics, epinephrine may precipitate or aggravate angina pectoris as well as produce ventricular arrhythmias. It should be recognized that the presence of these conditions is not a contraindication to epinephrine administration in an acute, life-threatening situation.

Epinephrine is light sensitive and should be stored in the carrier tube provided. Store at 25°C (77°F); excursions permitted to 15°C-30°C (59°F-86°F) (See USP Controlled Room Temperature). Do not refrigerate. Before using, check to make sure the solution in the auto-injector is not discolored. Replace the auto-injector if the solution is discolored or contains a precipitate.

PRECAUTIONS

(1) General

EpiPen® and EpiPen® Jr Auto-Injectors are not intended as a substitute for immediate medical care. In conjunction with the administration of epinephrine, the patient should seek immediate medical or hospital care. More than two sequential doses of epinephrine should only be administered under direct medical supervision.

Epinephrine is essential for the treatment of anaphylaxis. Patients with a history of severe allergic reactions (anaphylaxis) to insect stings or bites, foods, drugs, and other allergens as well as idiopathic and exercise-induced anaphylaxis should be carefully instructed about the circumstances under which epinephrine should be used. It must be clearly determined that the patient is at risk of future anaphylaxis, since the following risks may be associated with epinephrine administration (see DOSAGE and ADMINISTRATION).

Epinephrine should be used with caution in patients who have cardiac arrhythmias, coronary artery or organic heart disease, hypertension, or in patients who are on drugs that may sensitize the heart to arrhythmias, e.g., digitalis, diuretics, quinidine, or other antiarrhythmics. In such patients, epinephrine may precipitate or aggravate angina pectoris as well as produce ventricular arrhythmias.

The effects of epinephrine may be potentiated by tricyclic antidepressants and monoamine oxidase inhibitors.

Some patients may be at greater risk of developing adverse reactions after epinephrine administration. These include: hyperthyroid individuals, individuals with cardiovascular disease, hypertension, or diabetes, elderly individuals, pregnant women, pediatric patients under 30 kg (66 lbs.) body weight using EpiPen® Auto-Injector, and pediatric patients under 15 kg (33 lbs.) body weight using EpiPen® J r Auto-Injector.

Despite these concerns, epinephrine is essential for the treatment of anaphylaxis. Therefore, patients with these conditions, and/or any other person who might be in a position to administer EpiPen® or EpiPen® Jr Auto-Injector to a patient experiencing anaphylaxis should be carefully instructed in regard to the circumstances under which epinephrine should be used.

(2) Information for Patients

Complete patient information, including dosage, direction for proper administration and precautions can be found inside each EpiPen®/EpiPen® Jr Auto-Injector carton.

Epinephrine may produce symptoms and signs that include an increase in heart rate, the sensation of a more forceful heartbeat, palpitations, sweating, nausea and vomiting, difficulty breathing, pallor, dizziness, weakness or shakiness, headache, apprehension, nervousness, or anxiety. These symptoms and signs usually subside rapidly, especially with rest, quiet and recumbency. Patients with hypertension or hyperthyroidism may develop more severe or persistent effects, and patients with coronary artery disease could experience angina. Patients with diabetes may develop increased blood glucose levels following epinephrine administration. Patients with Parkinson's disease may notice a temporary worsening of symptoms.

In case of accidental injection, the patient should be advised to immediately go to the emergency room for treatment. Since the epinephrine in the EpiPen® Auto-Injector is a strong vasoconstrictor when injected into the digits, hands or feet, treatment should be directed at vasodilation if there is such an inadvertent administration to these areas (see ADVERSE REACTIONS).

(3) Drug Interactions

Patients who receive epinephrine while concomitantly taking cardiac glycosides or diuretics should be observed carefully for the development of cardiac arrhythmias.

The effects of epinephrine may be potentiated by tricyclic antidepressants, monoamine oxidase inhibitors, levothyroxine sodium, and certain antihistamines, notably chlorpheniramine, tripe-lennamine and diphenhydramine.

The cardiostimulating and bronchodilating effects of epinephrine are antagonized by beta-adrenergic blocking drugs, such as propranolol. The vasoconstricting and hypertensive effects of epinephrine are antagonized by alpha-adrenergic blocking drugs, such as phentoloamine. Ergot alkaloids may also reverse the pressor effects of epinephrine.

(4) Carcinogenesis, Mutagenesis, Impairment of Fertility

Epinephrine and other catecholamines have been shown to have mutagenic potential in vitro and to be an oxidative mutagen in a WP2 bacterial reverse mutation assay. Epinephrine had a moderate degree of mutagenicity, and was positive in the DNA Repair test with B. subtilis (REC) assay, but was not mutagenic in the Salmonella bacterial reverse mutation assay.
Studies of epinephrine after repeated exposure in animals to evaluate the carcinogenic and mutagenic potential or the effect on fertility have not been conducted. This should not prevent the use of epinephrine under the conditions noted under INDICATIONS AND USAGE.

(5) Usage in Pregnancy

Pregnancy Category C: There is no study on the acute effect of epinephrine on pregnancy. Epinephrine has been shown to have developmental effects when administered subcutaneously in rabbits at a dose of 1.2 mg/kg daily for two to three days (approximately 30 times the maximum recommended daily subcutaneous or intramuscular dose on a mg/m^2 basis), in mice at a subcutaneous dose of 1 mg/kg daily for 10 days (approximately 7 times the maximum daily subcutaneous or intramuscular dose on a mg/m^2 basis) and in hamsters at a subcutaneous dose of 0.5 mg/kg daily for 4 days (approximately 5 times the maximum recommended daily subcutaneous or intramuscular dose on a mg/m^2 basis). These effects were not seen in mice at a subcutaneous dose of 0.5 mg/kg daily for 10 days (approximately 3 times the maximum recommended daily subcutaneous or intramuscular dose on a mg/m^2 basis). Although, there are no adequate and well-controlled studies in pregnant women, epinephrine should be used in pregnancy only if the potential benefit justifies the potential risk to the fetus.

ADVERSE REACTIONS

Adverse reactions to epinephrine include transient, moderate anxiety; apprehensiveness; restlessness; tremor; weakness; dizziness; sweating; palpitations; pallor; nausea and vomiting; headache; and/or respiratory difficulties. These symptoms occur in some persons receiving therapeutic doses of epinephrine, but are more likely to occur in patients with hypertension or hyperthyroidism. Arrhythmias, including fatal ventricular fibrillation, have been reported in patients with underlying cardiac disease or certain drugs (see PRECAUTIONS, Drug Interactions). Rapid rises in blood pressure have produced cerebral hemorrhage, particularly in elderly patients with cardiovascular disease. Angina may occur in patients with coronary artery disease. The potential for epinephrine to produce these types of adverse reactions does not contraindicate its use in an acute life-threatening allergic reaction.

Accidental injection into the digits, hands or feet may result in loss of blood flow to the affected area (see WARNINGS). Adverse events experienced as a result of accidental injections may include increased heart rate, local reactions including injection site pallor, coldness and hypoaesthesia or injury at the injection site resulting in bruising, bleeding, discoloration, erythema or skeletal injury.

OVERDOSAGE

Epinephrine is rapidly inactivated in the body and treatment following overdose with epinephrine is primarily supportive. If necessary, pressor effects may be counteracted by rapidly acting vasodilators or alpha-adrenergic blocking drugs. If prolonged hypotension follows such measure, it may be necessary to administer another pressor drug.

Overdosage of epinephrine may produce extremely elevated arterial pressure, which may result in cerebrovascular hemorrhage, particularly in elderly patients.

Overdosage may also result in pulmonary edema because of peripheral vascular constriction together with cardiac stimulation. Treatment consists of a rapidly acting alpha-adrenergic blocking drug and/or respiratory support.

Epinephrine overdosage can also cause transient bradycardia followed by tachycardia and these may be accompanied by potentially fatal cardiac arrhythmias. Premature ventricular contractions may appear within one minute after injection and may be followed by multifocal ventricular tachycardia (prefibrillation rhythm). Subsidence of the ventricular effects may be followed by atrial tachycardia and occasionally by atrioventricular block. Treatment of arrhythmias consists of administration of a beta-blocking drug such as propranolol.

Overdosage sometimes results in extreme pallor and coldness of the skin, metabolic acidosis and kidney failure. Suitable corrective measures must be taken in such situations.

DOSAGE AND ADMINISTRATION

EpiPen® or EpiPen® Jr Auto-Injector prescribers should ensure that the patient or caregiver understands the indications and use of this product. A health care provider should review the patient instructions and operation of the EpiPen® or EpiPen® Jr Auto-Injector, in detail, with the patient or caregiver. Inject EpiPen® or EpiPen® Jr intramuscularly or subcutaneously into the anterolateral aspect of the thigh, through clothing if necessary. See detailed Directions for Use on the accompanying Patient Instructions.

Selection of the appropriate dosage strength is determined according to patient body weight.

EpiPen® Auto-Injector delivers 0.3 mg epinephrine injection (0.3 mL, 1:1000) and is intended for patients who weigh 30 kg or more (approximately 66 pounds or more).

EpiPen® Jr Auto-Injector delivers 0.15 mg epinephrine injection (0.3 mL, 1:2000) and is intended for patients who weigh 15 to 30 kg (33 - 66 pounds).

Each EpiPen® or EpiPen® Jr Auto-Injector contains a single dose of epinephrine. Since the doses of epinephrine delivered from EpiPen® or EpiPen® Jr Auto-Injector are fixed, consider using other forms of injectable epinephrine if doses lower than 0.15 mg are deemed necessary. The prescriber should carefully assess each patient to determine the most appropriate dose of epinephrine, recognizing the life-threatening nature of the reactions for which this drug is indicated. With severe persistent anaphylaxis, repeat injections with an additional EpiPen® Auto-Injector may be necessary.

Patients should be instructed to periodically visually inspect the epinephrine solution for particulate matter and discoloration. If the solution contains particulate matter or develops a pinkish color or becomes darker than slightly yellow, the patient should immediately contact their physician for a replacement, since these changes indicate that the effectiveness of the drug product may be decreased.

HOW SUPPLIED

EpiPen® Auto-Injectors (epinephrine injections, USR 1:1000, 0.3 mL) are available in individual cartons, NDC 49502-500-01, and as EpiPen 2-Pak®, NDC 49502-500-02, a pack that contains two EpiPen® Auto-Injectors (epinephrine injections, USP, 1:1000, 0.3 mL) and one EpiPen® Auto-Injector trainer device.

EpiPen® Jr Auto-Injectors (epinephrine injection, USP, 1:2000, 0.3 mL) are available in individual cartons, NDC 49502-501-01, and as EpiPen Jr 2-Pak®, NDC 49502-501-02, a pack that contains two EpiPen® Jr Auto-Injectors (epinephrine injections, USP, 1:2000, 0.3 mL) and one EpiPen® Auto-Injector trainer device.

EpiPen 2-Pak® and EpiPen Jr 2-Pak® also includes a S-clip to clip two cases together.

Store at 25°C (77°F); excursions permitted to 15°C-30°C (59°F-86°F) (See USP Controlled Room Temperature).
Contains no latex. Protect from light.

Rx only.

MANUFACTURED FOR Dey, LP.,
NAPA, CALIFORNIA 94558, U.S.A.
by Meridian Medical Technologies, Inc.,
a subsidiary of King Pharmaceuticals®, Inc.,
Columbia, MD 21046, U.S.A.

EpiPen®, EpiPen® Jr, EpiPen 2-Pak®, and EpiPen Jr 2-Pak® are registered trademarks of Mylan, Inc. licensed exclusively to its wholly-owned affiliate, Dey, LP. of Napa California, USA.

09/08
0001497
03-914-00

PATIENT INSERT

EpiPen®
(epinephrine) Auto-Injector 0.3 mg
EpiPen® = one dose of 0.30 mg epinephrine (USP, 1:1000, 0.3 mL)

EpiPen® JR
(epinephrine) Auto-Injector 0.15 mg
EpiPen® Jr = one dose of 0.15 mg epinephrine (USP, 1:2000, 0.3 mL)

Pharmacist - Please Dispense this Leaflet with Product

IMPORTANT INFORMATION

The patient and caregiver should read this information carefully before using EpiPen® or EpiPen® Jr Auto-Injector. Please be prepared! Read the entire insert before an emergency occurs! EpiPen® and EpiPen® Jr Auto-Injectors are disposable, prefilled automatic injection devices for use during allergic emergencies. They contain a single dose of epinephrine which you inject into your outer thigh. EpiPen® and EpiPen® Jr Auto-Injector contain no latex. The EpiPen® and EpiPen®Jr Auto-Injectors are intended for people who have been prescribed this medication by their physician.

It's important that you have this emergency medicine with you at all times. If you need additional units to keep at work, school, etc, please talk to your doctor. This information does not take the place of talking with your doctor about your medical condition or your treatment.

What is the most important information I should know about EpiPen® and EpiPen® Jr Auto-Injector?

When you have allergic reaction (anaphylaxis) use the EpiPen® or EpiPen® Jr Auto-Injector right away and immediately go to your doctor or emergency room for more medical treatment.

- It is important not to be afraid to use the EpiPen® or EpiPen® Jr Auto-Injector for emergency treatment of allergic reactions (anaphylaxis). For most people, injection of the EpiPen® or EpiPen® Jr Auto-Injector in the thigh does not hurt, and use of the EpiPen® or EpiPen® Jr Auto-Injector early at the start of such allergic reactions is important to help prevent the allergic reaction from becoming worse.
- Inject EpiPen® or EpiPen® Jr Auto-Injector into the middle of the outer side of the thigh (upper leg).
- Epinephrine, the active ingredient in EpiPen® and EpiPen® Jr Auto-Injectors is used to treat life-threatening allergic reactions (anaphylaxis). You should use this medication only if your doctor has prescribed it for allergic emergencies. Such emergencies may occur from insect stings or bites, foods, drugs, latex, other allergens, exercise induced anaphylaxis, or unknown causes.
- Make sure to tell your doctor about all your medical conditions and allergies.
- Always get medical treatment immediately after using EpiPen® or EpiPen® Jr Auto-Injector.

Since you cannot predict when a life-threatening allergic reaction may occur, carry the EpiPen® or EpiPen® Jr Auto-Injector with you at all times.

What is EpiPen®/EpiPen® Jr Auto-Injector?

The EpiPen® and EpiPen® Jr Auto-Injectors are products used for the emergency injection of epinephrine. Epinephrine is a medicine used for life-threatening allergic reactions such as severe swelling, breathing problems, or loss of blood pressure. Allergic reactions can be caused by stinging and biting insects, allergy injections, food, medicines, exercise, or unknown causes.

Life-threatening allergic reactions may show up as closing of your breathing airways, wheezing, sneezing, hoarseness, hives, itching, swelling, skin redness, fast heartbeat, weak pulse, feeling very anxious, confusion, stomach pain, losing control of urine or bowel movements (incontinence), faintness, or "passing out" (unconsciousness).

The EpiPen® Auto-Injector (0.3 mg) is generally intended for patients who weigh 66 pounds or more (30 kilograms or more).

The EpiPen® Jr Auto-Injector (0.15 mg) is generally intended for patients who weigh approximately 33 to 66 pounds (15 to 30 kilograms).

Who should not use EpiPen®/EpiPen® Jr Auto-Injector?

There are no absolute contraindications to the use of EpiPen® and EpiPen® Jr Auto-Injector in a life-threatening allergic reaction. People with certain medical conditions have a higher chance of having serious side effects from EpiPen® or EpiPen® Jr Auto-Injector.

Tell your doctor and pharmacist about all your medical conditions, but especially if you:

- Have heart disease or high blood pressure
- Have diabetes
- Have thyroid conditions
- Are pregnant

Tell your doctor about all the medicines you take, including prescription and non-prescription medicines, vitamins and herbal supplements. Inform your doctor of all known allergies. Some medicines may cause serious side effects if taken while you use EpiPen®/EpiPen® Jr Auto-Injector. Some medicines may affect how EpiPen®/EpiPen® Jr Auto-Injector works.

EpiPen® or EpiPen" Jr Auto-Injector may affect how your other medicines work.

What should I avoid while using EpiPen®/EpiPen® Jr Auto-Injector?

- NEVER PUT THUMB, FINGERS OR HAND OVER ORANGE TIP. NEVER PRESS OR PUSH ORANGE TIP WITH THUMB, FINGERS OR HAND. The needle comes out of orange tip. Accidental injection into finger, hands or feet may result in loss of blood flow to these areas. If this happens, go immediately to the nearest emergency room.
- Do not inject EpiPen® or EpiPen® Jr Auto-Injector into the buttock or any other part of the body, other than the middle of the outer side of your thigh (upper leg).
- Do not inject EpiPen® or EpiPen® Jr Auto-Injector into a vein.
- Do not drop carrier tube or auto-injector. If carrier tube or auto-injector is dropped, inspect for damage and leakage. Discard auto-injector and carrier tube, and replace if damage or leakage is noticed or suspected.

What are the possible side effects of EpiPen®/ EpiPen® Jr Auto-Injector?

Too much epinephrine can cause dangerous high blood pressure or stroke.

If you take certain medicines, you may develop serious life-threatening side effects from the epinephrine in EpiPen®/ EpiPen® Jr Auto-Injector. Be sure to tell your doctor all the medicines you take, especially medicines for asthma.

Patients with certain medical conditions, or who take certain medicines, may get more side effects from EpiPen®/ EpiPen® Jr Auto-Injector or the side effects may last longer. This includes patients who take certain types of medicines for asthma, allergies, depression, low thyroid, high blood pressure, and heart disease. Patients with heart disease may feel chest pain (angina).

EpiPen®/EpiPen® Jr Auto-Injector (epinephrine) can cause the following reactions. Some reactions can be serious. They usually go away with rest. Please notify your doctor if you experience any of these.

Common side effects of EpiPen®/EpiPen® Jr Auto-Injector include:

- Faster, irregular (wrong) or "pounding" heartbeat
- Sweating
- Nausea and vomiting
- Breathing problems
- Paleness
- Dizziness
- Weakness or shakiness
- Headache
- Feelings of over excitement, nervousness or anxiety

These are not all the possible side effects of
EpiPen®/EpiPen® Jr Auto-Injector.
For more information, ask your doctor or pharmacist.
Call your doctor for medical advice about side effects.
You may report side effects to FDA at 1-800-FDA-1088.

How should I store EpiPen® /EpiPen® Jr Auto-Injector?

- Keep the EpiPen® and EpiPen® Jr Auto-Injector nearby and ready for use at all times.
- Store at 25°C (77°F); excursions permitted to 15°C-30°C (59°F-86°F) (See USP Controlled Room Temperature). Contains no latex. Protect from light.
- Do NOT store in refrigerator.
- Do NOT expose to extreme cold or heat. For example, do NOT store in your vehicle's glove box.
- Examine contents in clear window of auto-injector periodically. If the solution is discolored or contains solid particles (precipitate), replace the unit. Solution should be clear.
- Always keep your EpiPen ® or EpiPen ® Jr Auto- Injector in the carrier tube with the blue safety release on until you need to use it.
  Your auto-injector has an expiration date
- Example:"DEC 08" = December 31, 2008
- Replace it before the expiration date.

SEE OTHER SIDE FOR "DIRECTIONS FOR USE" AND FOR EPIPEN® CENTER FOR ANAPHYLACTIC SUPPORT™

FREE ENROLLMENT FORM.

DIRECTIONS FOR USE

- REMOVE AUTO-INJECTOR FROM CARRIER TUBE BEFORE USE.
- NEVER PUT THUMB, FINGERS OR HAND OVER ORANGE TIP.
- NEVER PRESS OR PUSH ORANGE TIP WITH THUMB, FINGERS OR HAND.
- THE NEEDLE COMES OUT OF ORANGE TIP.
- DO NOT REMOVE BLUE SAFETY RELEASE UNTIL READY TO USE.
- DO NOT USE IF SOLUTION IS DISCOLORED.
- DO NOT PLACE PATIENT INSERT OR ANY OTHER FOREIGN OBJECTS IN CARRIER WITH AUTO-INJECTOR, AS THIS MAY PREVENT YOU FROM REMOVING THE AUTO-INJECTOR FOR USE.

TO REMOVE AUTO-INJECTOR FROM THE CARRIER TUBE:

1. Flip open the yellow cap of the EpiPen® or the green cap of theEpiPen® Jr Auto-Injector carrier tube.
2. Remove the EpiPen® or EpiPen® Jr Auto-Injector by tipping and sliding it out of the carrier tube.

TO USE AUTO-INJECTOR:

1. Grasp unit with the orange tip pointing downward.
2. Form fist around the unit (orange tip down).
3. With your other hand, pull off the blue safety release.
4. Hold orange tip near outer thigh.
  DO NOT INJECT INTO BUTTOCK.
5. Swing and firmly push against outer thigh until it clicks so that unit is perpendicular (at 90° angle) to the thigh.
  (Auto-injector is designed to work through clothing.)
6. Hold firmly against thigh for approximately 10 seconds to deliver drug. (The injection is now complete. The window on auto-injector will be obscured.)
7. Remove unit from thigh (the orange needle cover will extend to cover needle) and massage injection area for 10 seconds.
8. Call 911 and seek immediate medical attention.
9. Take the used auto-injector with you to the hospital emergency room.

Note: Most of the liquid (about 85%) stays in the auto-injector and cannot be reused. However, you have received the correct dose of the medication if the orange needle tip is extended and the window is obscured. Trainer label has blue background color. Blue background labeled trainer contains no needle and no drug.

! WARNING !

- NEVER put thumb, fingers or hand over orange tip. NEVER press or push orange tip with thumb, fingers or hand. The needle comes out of orange tip. Accidental injection into hands or feet may result in loss of blood flow to these areas. If this happens, go immediately to the nearest emergency room.
- EpiPen® and EpiPen® Jr Auto-Injector should be injected only into the outer thigh (see "Directions for Use"). DO NOT INJECT INTO BUTTOCK.
- Do NOT remove blue safety release until ready to use.

To dispose of expired units

- Expired auto-injectors must be disposed of properly.
- To dispose of an expired auto-injector and carrier tube, take them to your doctor's office or to a hospital for proper disposal.
- Used auto-injector with extended needle cover will not fit in carrier tube.

IMMEDIATELY AFTER USE

- Go immediately to the nearest hospital emergency room or call 911.
  You may need further medical attention. Take your used auto-injector with you.
- Tell the doctor that you have received an injection of epinephrine in your thigh.
- Give your used EpiPen®/EpiPen® Jr Auto-Injector to the doctor for inspection and proper disposal.

Do not attempt to take the auto-injector apart.

Manufactured for Dey, L.P., Napa, CA 94558 USA.
by Meridian Medical Technologies™, Inc.
Columbia, MD 21046 USA.

A subsidiary of King Pharmaceuticals® Inc.

EpiPen® is a registered trademark of Mylan, Inc. licensed exclusively to its wholly-owned affiliate, Dey, LP. of Napa California, USA

Design and Utility patents applied for Carrier Tube and Auto-Injector design platform.
©2008 by Meridian Medical Technologies™, Inc.
04/2008
03-855-00
0001496

SEE OTHER SIDE FOR MORE INFORMATION.

PACKAGE LABEL – PRINCIPAL DISPLAY PANEL – EpiPen 2-Pak 0.3 mg CARTON

NDC 55045-3207-02

Rx only.